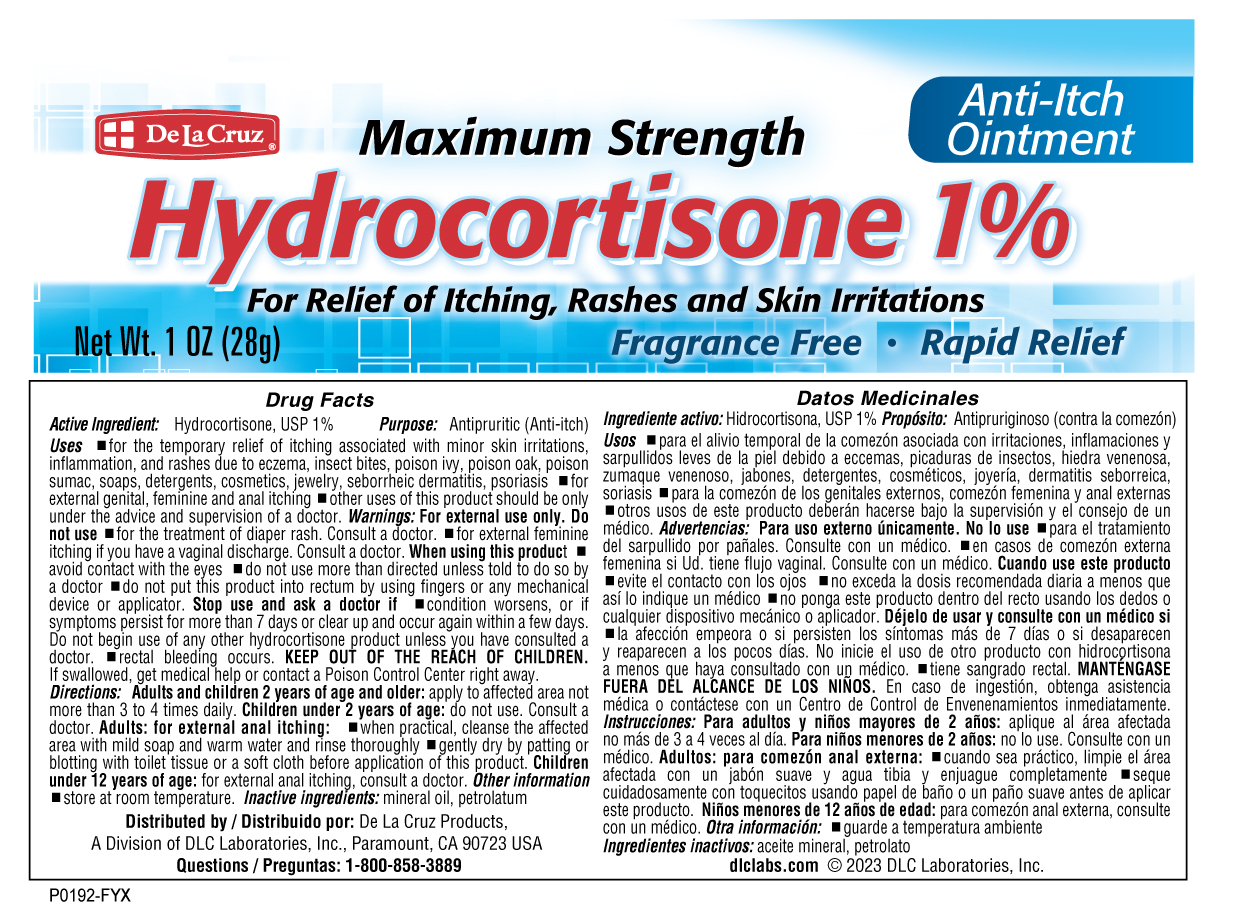 DRUG LABEL: Maximum Strength Hydrocortisone
NDC: 24286-1560 | Form: OINTMENT
Manufacturer: DLC Laboratories, Inc
Category: otc | Type: HUMAN OTC DRUG LABEL
Date: 20260107

ACTIVE INGREDIENTS: HYDROCORTISONE 1 g/100 g
INACTIVE INGREDIENTS: MINERAL OIL; PETROLATUM

Maximum Strength Hydrocortisone 1%

Drug Facts

Active ingredient

Hydrocortisone, USP 1%

Purpose

Antipruritic (Anti-itch)

Uses

- for the temporary relief of itching associated with minor skin irritations, inflammation, and rashes due to eczema, insect bites, poison ivy, poison oak, poison sumac, soaps, detergents, cosmetics, jewelry, seborrheic dermatitis, psoriasis
- for external genital, feminine and anal itching
- other uses of this product should be only under the advice and supervision of a doctor

Warnings

For external use only

Do not use

- for the treatment of diaper rash. Consult a doctor.
- for external feminine itching if you have a vaginal discharge. Consult a doctor.

When using this product

- avoid contact with the eyes
- do not use more than directed unless told to do so by a doctor
- do not put this product into rectum by using fingers or any mechanical device or applicator

Stop use and ask a doctor if

- condition worsens, or if symptoms persist for more than 7 days or clear up and occur again within a few days. Do not begin use of any other hydrocortisone product unless you have consulted a doctor.
- rectal bleeding occurs

KEEP OUT OF REACH OF CHILDREN

KEEP OUT OF THE REACH OF CHILDREN. If swallowed, get medical help or contact a Poison Control Center right away.

Directions

Adults and children 2 years of age and older: apply to affected area not more than 3 to 4 times daily.

Children under 2 years of age: do not use. Consult a doctor.

Adults: for external anal itching:

- when practical, cleanse the affected area with mild soap and warm water and rinse thoroughly
- gently dry by patting or blotting with toilet tissue or a soft cloth before application of this product

Children under 12 years of age: for external anal itching, consult a doctor

Other information

- store at room temperature

Inactive ingredients

mineral oil, petrolatum

Questions

1-800-858-3889

Distributed by:

De La Cruz Products
A Division of DLC Laboratories, Inc.
Paramount, CA 90723 USA

PRINCIPAL DISPLAY PANEL - 28 g Tube Box

De La Cruz®

Anti-Itch
Ointment

Maximum Strength

Hydrocortisone 1%

For Relief of Itching, Rashes
and Skin Irritations

- Fragrance Free
- Rapid Relief

Net Wt. 1 OZ (28g)